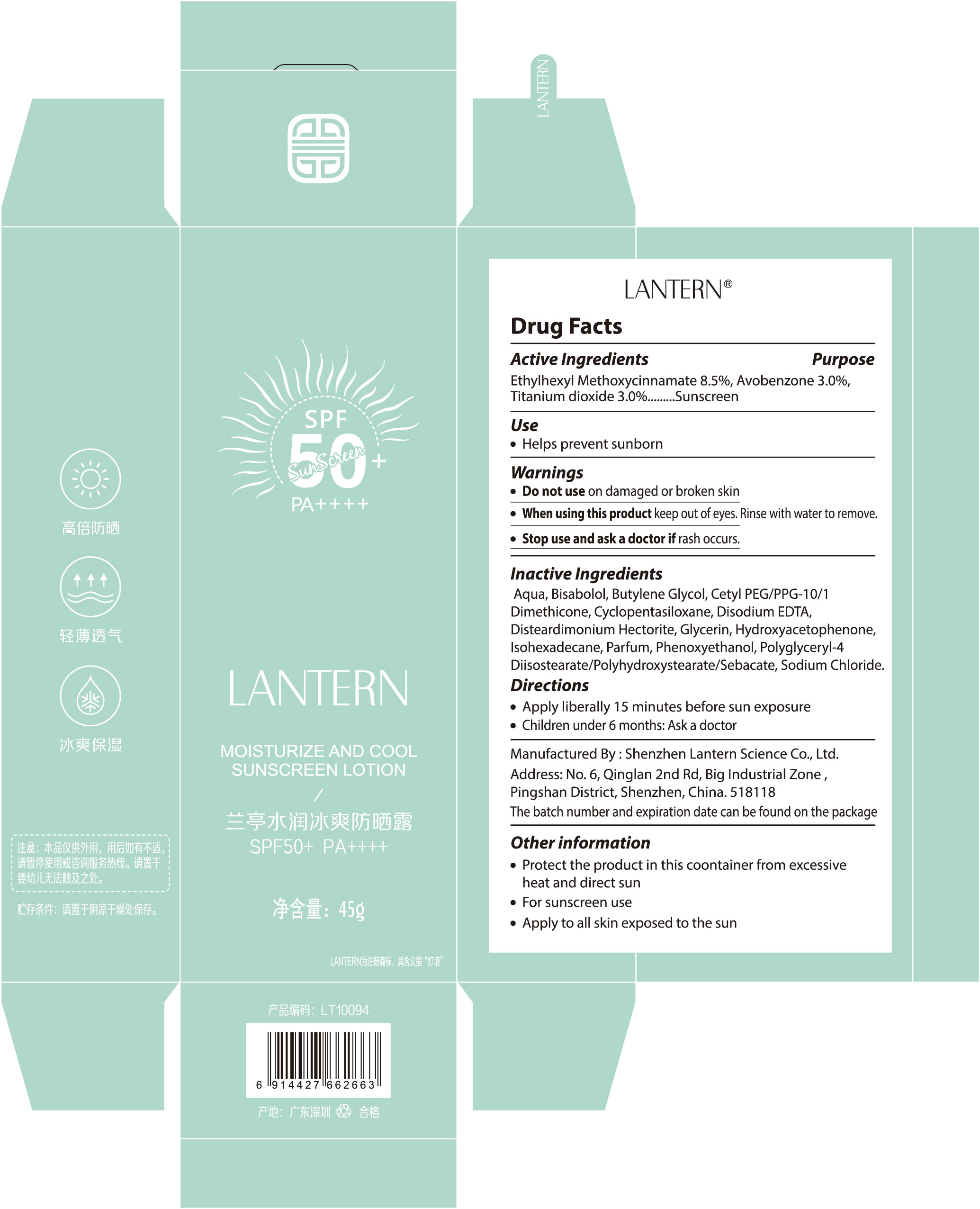 DRUG LABEL: LANTERN SUNSCREEN SPF50
NDC: 54860-416 | Form: PASTE
Manufacturer: Shenzhen Lantern Scicence Co.,Ltd.
Category: otc | Type: HUMAN OTC DRUG LABEL
Date: 20231018

ACTIVE INGREDIENTS: TITANIUM DIOXIDE 3 g/100 g; AVOBENZONE 3 g/100 g; OCTINOXATE 8.5 g/100 g
INACTIVE INGREDIENTS: DECYL GLUCOSIDE 0.375 g/100 g; WATER 59.31 g/100 g; ALPHA-TOCOPHEROL ACETATE 0.3 g/100 g; XANTHAN GUM 0.01 g/100 g; PEG-20 METHYL GLUCOSE SESQUISTEARATE 0.8 g/100 g; AMMONIUM ACRYLOYLDIMETHYLTAURATE/VP COPOLYMER 0.8 g/100 g; PROPYLENE GLYCOL 0.02 g/100 g; GLYCERIN 5 g/100 g; DIETHYLAMINO HYDROXYBENZOYL HEXYL BENZOATE 4.5 g/100 g; DIMETHICONE 20 2 g/100 g; PHENOXYETHANOL 0.3 g/100 g

MOISTURIZE AND COOLSUNSCREEN LOTION SPF50

Drug Facts

Active Ingredient

ETHYLHEXYL METHOXYCINNAMATE：8.5%

Avobenzone：3.0%

Titanium dioxide：3.0% Sunscreen

Inactive ingredients

AQUA, METHYLENE BIS-BENZOTRIAZOLYL TETRAMETHYLBUTYLPHE NOL, AQUA, DECYL GLUCOSIDE, PROPYLENE GLYCOL, XANTHAN GUM, GLYCERIN, DIETHYLAMINO HYDROXYBENZOYL HEXYL BENZOATE, BIS-ETHYLHEXYLOXYPHENOL METHOXYPHENYL TRIAZINE, ETHYLHEXYL TRIAZONE, DIMETHICONE, PEG-20 METHYL GLUCOSE SESQUISTEARATE, AMMONIUM ACRYLOYLDIMETHYLTAURATE/VP COPOLYMER, METHYL GLUCOSE SESQUISTEARATE, PHENOXYETHANOL, TOCOPHERYL ACETATE, PARFUM, MENTHOL, METHYLPARABEN, BISABOLOL, ALLANTOIN, PROPYLPARABEN, DISODIUM EDTA, SPIRULINA PLATENSIS EXTRACT, SODIUM HYALURONATE.

Directions

Apply liberally 15 minutes before sunexposure.
Use a water resistant sunscreen if swimming or sweating.
Reapply at least every 2 hours.
Children under 6 months: Ask a docto

When using this product

Keep out of reach of children.
If product is swallowed, get medical help or contact a Poison Control Center rightaway

Purpose

Sunscreen

Stop use and ask a doctor

if rash occurs.

Do not use

On damaged or broken skin.
When using this product keep out of eyes.
Rinse with water to remove

Other information

Protect this product from excessive heat and direct sunlight

warnings

For external use only.

Keep out of reach of children

If product is swallowed, get medical help or contact a Poison Control Center rightaway.

Dosage & administration section

Apply liberally 15 minutes before sunexposure.
Use a water resistant sunscreen if swimming or sweating.
Reapply at least every 2 hours.
Children under 6 months: Ask a docto

package

Packaging